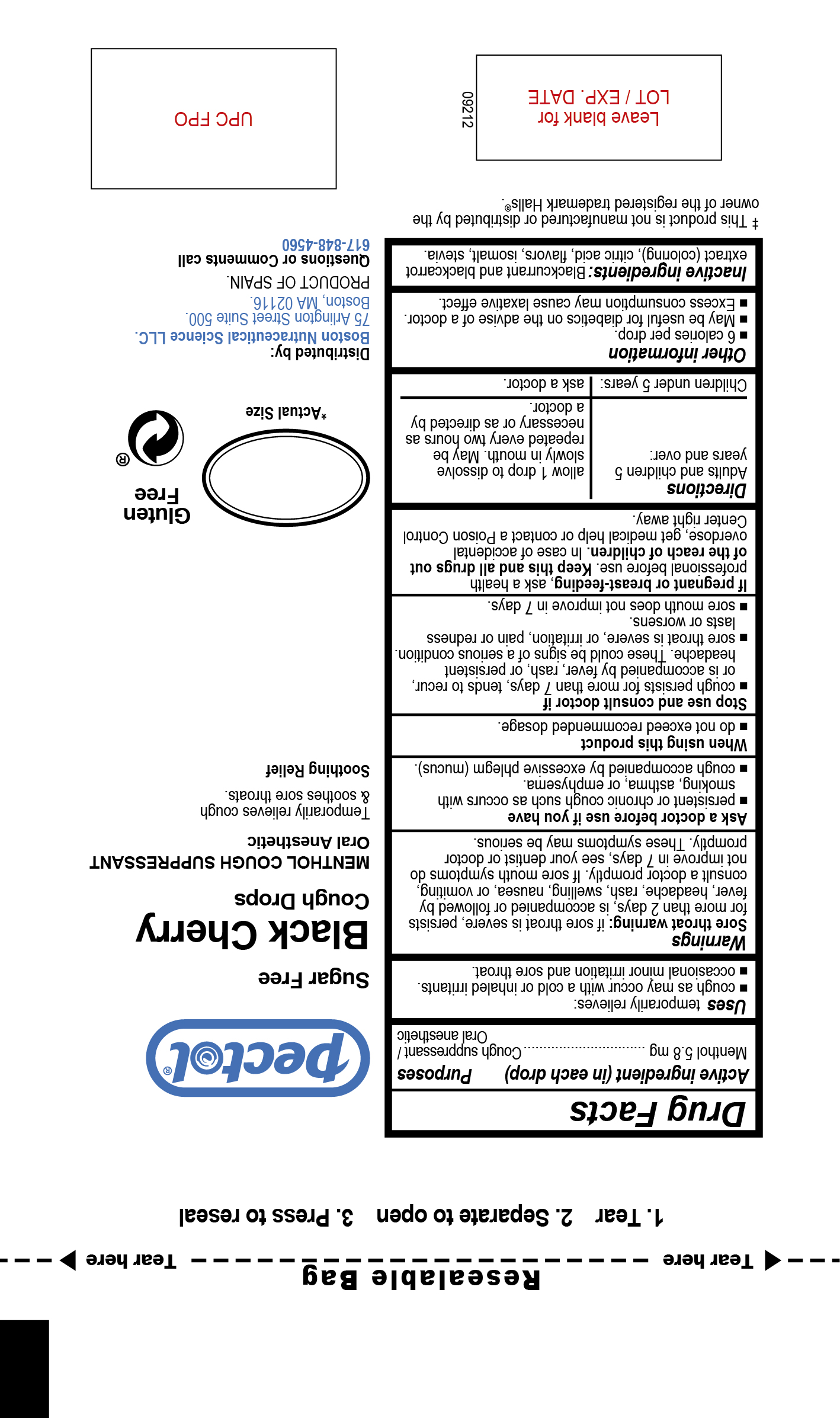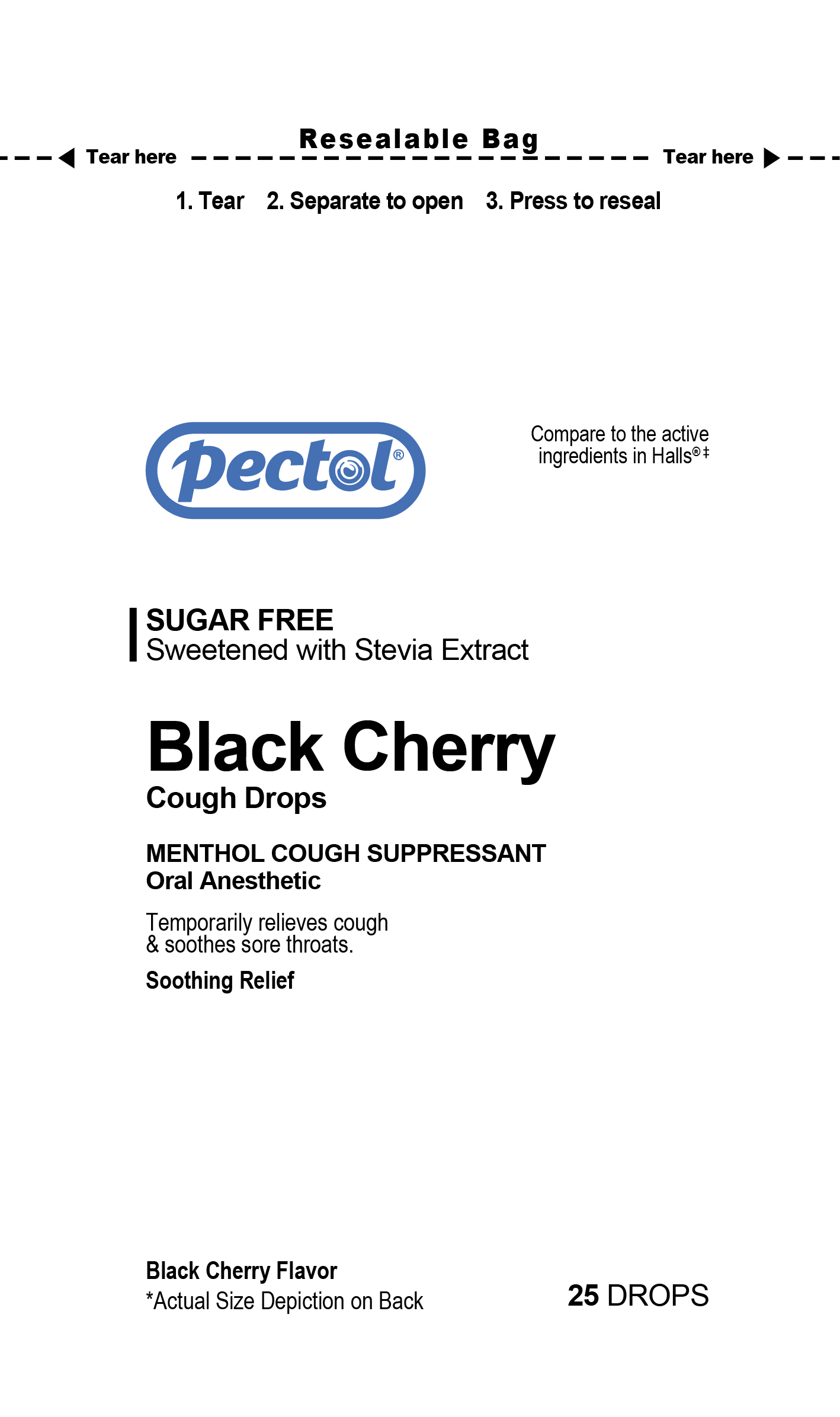 DRUG LABEL: Black Cherry Cough Drops
NDC: 72628-104 | Form: PASTILLE
Manufacturer: Boston Nutraceutical Production SL
Category: otc | Type: HUMAN OTC DRUG LABEL
Date: 20241007

ACTIVE INGREDIENTS: MENTHOL 5.8 mg/1 1
INACTIVE INGREDIENTS: BLACK CARROT; CHERRY; ISOMALT; WATER; ANHYDROUS CITRIC ACID; STEVIA REBAUDIANA WHOLE; BLACK CURRANT

Black Cherry Cough Drops
Sugar Free
Sweetened with Stevia Extract
25 drops

Active Ingredient in each drop Purposes

Menthol 5.8 mg Cough Suppressant

Oral anesthetic

Purposes

Cough suppressant/

Oral anesthetic

INDICATIONS AND USAGE

Uses Temporarily relieves:

- cough as may occur with cold or inhaled irritants
- ocassional minor irritations and sore throat

Warnings

Sore throat warning: if sore throat is severe, persists for more than 2 days, is accompanied or followed by fever, headache, rash, swealing, nausea, or vomiting, consult a doctor promptly. If sore mouth symptoms do not improve in 7 days, see your dentist or doctor promptly. These symptons may be serious.

Ask a doctor before use if you have

persistent or chronic cough such as occurs with smoking, asthma, or emphysema

cough accompanied by excessvie phlegm (mucus)

Stop use and consult doctor if

- cough persists for more than 7 days, tends to recur, or is accompanied by fever, rash, or persistent headache. These could be signs of a serious condition.
- sore throat is severe, or irritation, pain or redness last or worsens
- sore mouth does not improve in 7 days

PREGNANCY OR BREAST FEEDING

If pregnant or breast-feeding, ask a health professional before use.

KEEP OUT OF REACH OF CHILDREN

Keep this and all drugs out of the reach of children.

OVERDOSAGE

In case of accidental overdose, get medical help or contact a Poison Control Center right away.

Directions

- Adults and children 5 years and over: allow 1 drop to dissolve slowly in mouth. May be repeated every two hours as necessary or as directed by a doctor.
- Children under 5 years: ask a doctor

Other information

- 6 calories per drop
- May be useful for diabetics on the advise of a doctor
- Excessive consumption may cause laxative effect

INACTIVE INGREDIENT

Citric acid, isomalt, stevia, flavor cherry extract, colorant black currant and black carrot extract, water

Questions or comments call: 617-848-4560